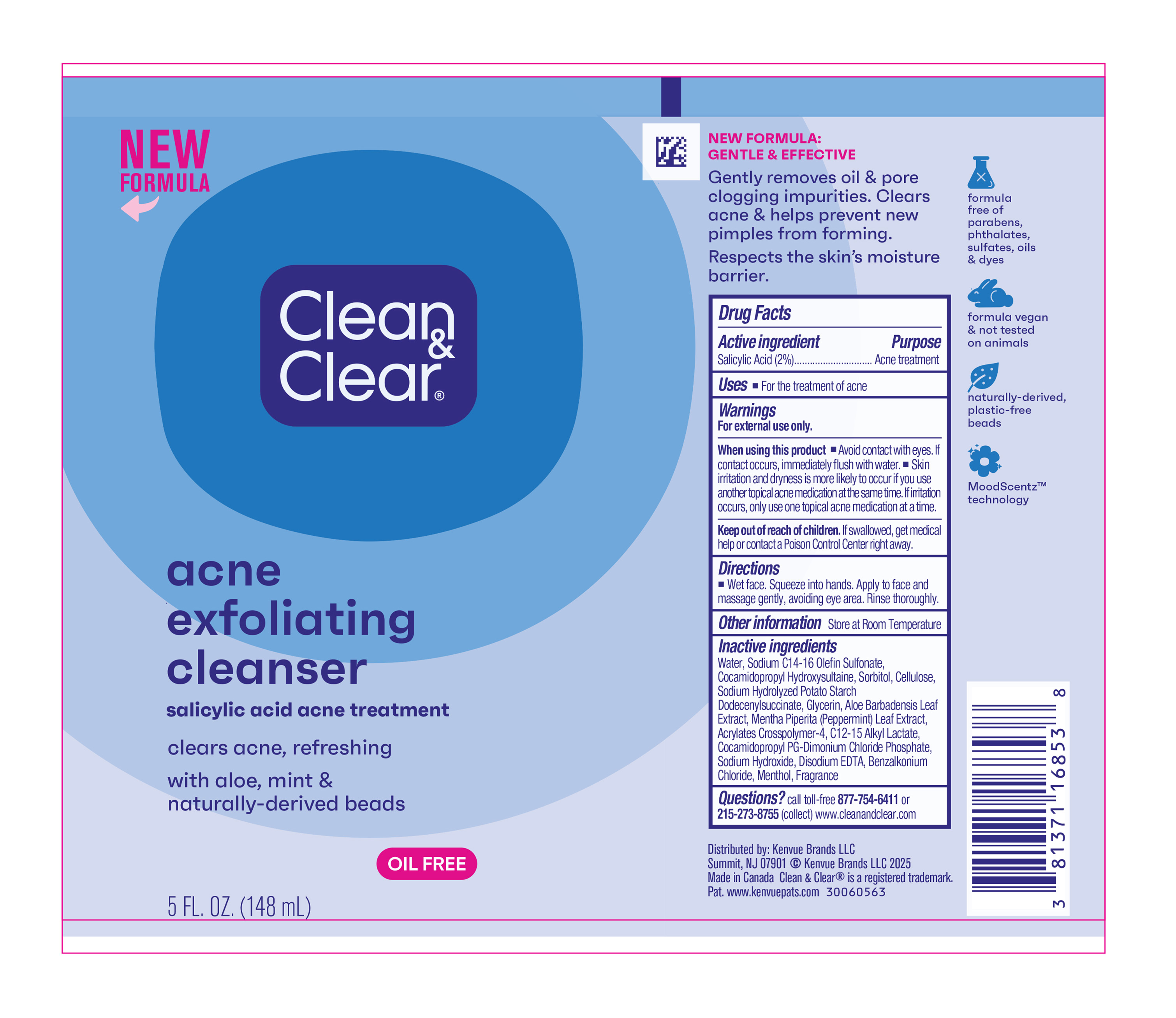 DRUG LABEL: Clean and Clear Acne Exfoliating Cleanser
NDC: 69968-0822 | Form: LIQUID
Manufacturer: Kenvue Brands LLC
Category: otc | Type: HUMAN OTC DRUG LABEL
Date: 20250728

ACTIVE INGREDIENTS: SALICYLIC ACID 20 mg/1 mL
INACTIVE INGREDIENTS: SODIUM C14-16 OLEFIN SULFONATE; SODIUM HYDROLYZED POTATO STARCH DODECENYLSUCCINATE; ALOE VERA LEAF; C12-15 ALKYL LACTATE; ACRYLATES CROSSPOLYMER-4; WATER; GLYCERIN; POWDERED CELLULOSE; SODIUM HYDROXIDE; EDETATE DISODIUM ANHYDROUS; BENZALKONIUM CHLORIDE; COCAMIDOPROPYL PG-DIMONIUM CHLORIDE PHOSPHATE; MENTHA PIPERITA LEAF; SORBITOL; COCAMIDOPROPYL HYDROXYSULTAINE; MENTHOL

Clean and Clear Acne Exfoliating Cleanser

Drug Facts

Active ingredient

Salicylic Acid (2%)

Purpose

Acne treatment

Uses

- For the treatment of acne

Warnings

For external use only.

When using this product

▪ Avoid contact with eyes. If contact occurs, immediately flush with water.

▪ Skin irritation and dryness is more likely to occur if you use another topical acne medication at the same time. If irritation occurs, only use one topical acne medication at a time.

Keep out of reach of children. If swallowed, get medical help or contact a Poison Control Center right away.

Directions

▪ Wet face. Squeeze into hands. Apply to face and massage gently, avoiding eye area. Rinse thoroughly.

Other Information

Store at Room Temperature

Inactive ingredients

Water, Sodium C14-16 Olefin Sulfonate, Cocamidopropyl Hydroxysultaine, Sorbitol, Cellulose, Sodium Hydrolyzed Potato Starch Dodecenylsuccinate, Glycerin, Aloe Brabadensis Leaf Extract, Mentha Piperita (Peppermint) Leaf Extract, Acrylates Crosspolymer-4, C12-15 Alkyl Lactate, Cocamidopropyl PG-Dimonium Chloride Phosphate, Sodium Hydroxide, Disodium EDTA, Benzalkonium Chloride, Menthol, Fragrance

Questions?

call toll-free 877-754-6411 or 215-273-8755 (collect) www.cleanandclear.com

Distributed by:

Kenvue Brands LLC
Summit, NJ 07901

PRINCIPAL DISPLAY PANEL - 148 mL Tube Label

NEW

FORMULA

Clean

&

Clear®

acne

exfoliating

cleanser

salicylic acid acne treatment

clears acne, refreshing

with aloe, mint &

naturally-derived beads

OIL FREE

5 FL. OZ. (148 mL)